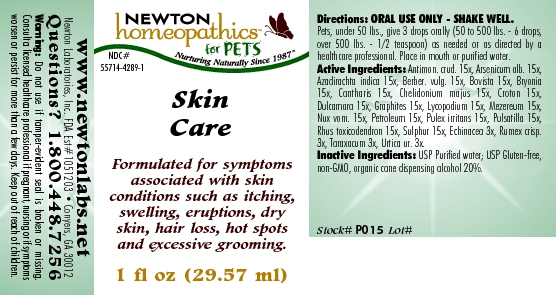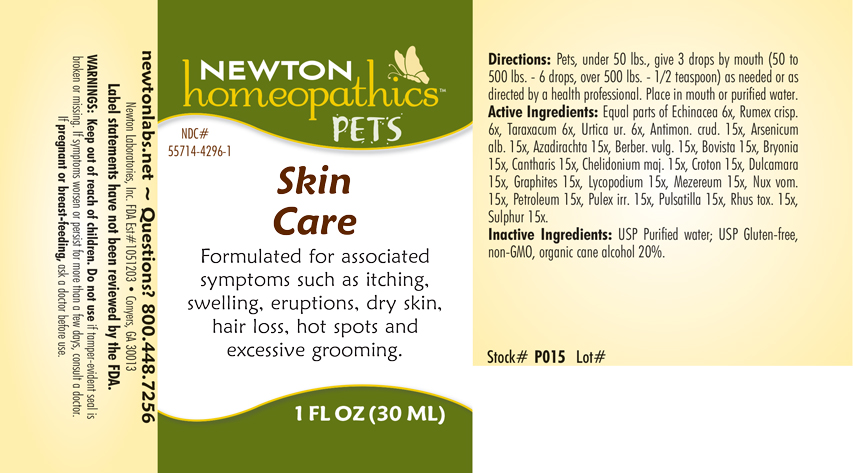 DRUG LABEL: Skin Care
NDC: 55714-4289 | Form: LIQUID
Manufacturer: Newton Laboratories, Inc.
Category: homeopathic | Type: OTC ANIMAL DRUG LABEL
Date: 20190114

ACTIVE INGREDIENTS: Antimony Trisulfide 15 [hp_X]/1 mL; Arsenic Trioxide 15 [hp_X]/1 mL; Azadirachta Indica Bark 15 [hp_X]/1 mL; Berberis Vulgaris Root Bark 15 [hp_X]/1 mL; Giant Puffball 15 [hp_X]/1 mL; Bryonia Alba Root 15 [hp_X]/1 mL; Lytta Vesicatoria 15 [hp_X]/1 mL; Chelidonium Majus 15 [hp_X]/1 mL; Croton Tiglium Seed 15 [hp_X]/1 mL; Solanum Dulcamara Top 15 [hp_X]/1 mL; Graphite 15 [hp_X]/1 mL; Lycopodium Clavatum Spore 15 [hp_X]/1 mL; Daphne Mezereum Bark 15 [hp_X]/1 mL; Strychnos Nux-vomica Seed 15 [hp_X]/1 mL; Kerosene 15 [hp_X]/1 mL; Pulex Irritans 15 [hp_X]/1 mL; Pulsatilla Vulgaris 15 [hp_X]/1 mL; Toxicodendron Pubescens Leaf 15 [hp_X]/1 mL; Sulfur 15 [hp_X]/1 mL; Echinacea, Unspecified 3 [hp_X]/1 mL; Rumex Crispus Root 3 [hp_X]/1 mL; Taraxacum Officinale 3 [hp_X]/1 mL; Urtica Urens 3 [hp_X]/1 mL
INACTIVE INGREDIENTS: Alcohol

Skin Care

INDICATIONS & USAGE SECTION

Formulated for symptoms associated with skin conditions such as itching, swelling, eruptions, dry skin, hair loss, hot spots and excessive grooming.

DOSAGE & ADMINISTRATION SECTION

Directions: Pets, under 50 lbs., give 3 drops by mouth (50 to 500 lbs. - 6 drops, over 500 lbs. - 1/2 teaspoon) as needed or as directed by a health professional. Place in mouth or purified water.

OTC - ACTIVE INGREDIENT SECTION

Equal parts of Echinacea 6x, Rumex crisp. 6x, Taraxacum 6x, Urtica ur. 6x, Antimon. crud. 15x, Arsenicum alb. 15x, Azadirachta indica 15x, Berber. vulg. 15x, Bovista 15x, Bryonia 15x, Cantharis 15x, Chelidonium majus 15x, Croton 15x, Dulcamara 15x, Graphites 15x, Lycopodium 15x, Mezereum 15x, Nux vom. 15x, Petroleum 15x, Pulex irritans 15x, Pulsatilla 15x, Rhus toxi. 15x, Sulphur 15x.

OTC - PURPOSE SECTION

Formulated for symptoms associated with skin conditions such as itching, swelling, eruptions, dry skin, hair loss, hot spots and excessive grooming.

INACTIVE INGREDIENT SECTION

Inactive Ingredients: USP Purified Water; USP Gluten-free, non-GMO, organic cane alcohol 20%.

QUESTIONS SECTION

newtonlabs.net Questions? 1.800.448.7256
Newton Laboratories, Inc. FDA Est # 1051203 - Conyers, GA 30013

WARNINGS SECTION

Warning: Do not use if tamper-evident seal is broken or missing. If symptoms worsen or persist for more than a few days, consult a doctor. If pregnant or breast-feeding, ask a doctor before use.

OTC - PREGNANCY OR BREAST FEEDING SECTION

If pregnant or breast-feeding, ask a doctor before use.

OTC - KEEP OUT OF REACH OF CHILDREN SECTION

Keep out of reach of children.